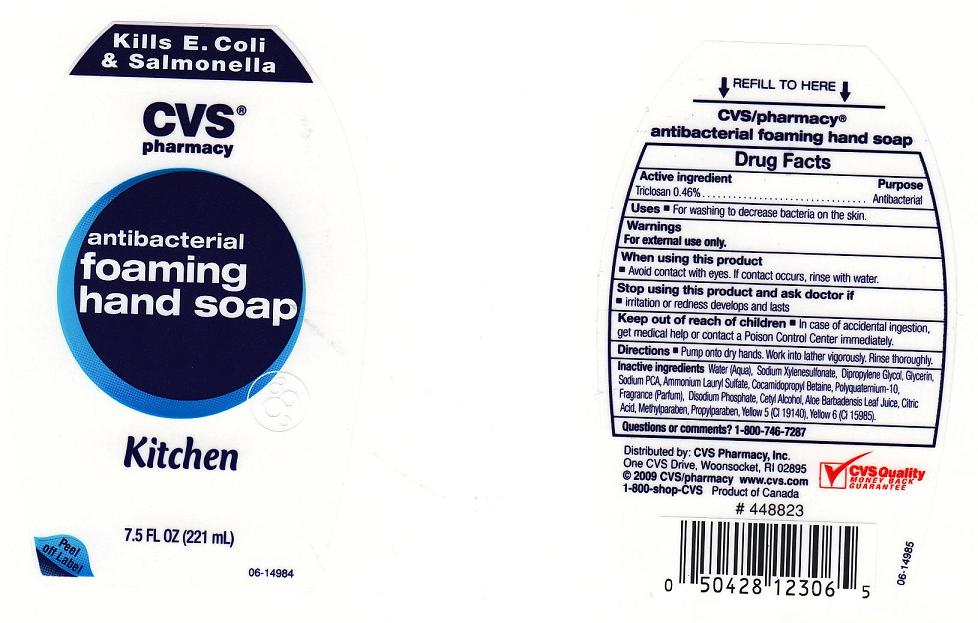 DRUG LABEL: CVS Antibacterial Foaming 
NDC: 59779-160 | Form: SOAP
Manufacturer: CVS Pharmacy
Category: otc | Type: HUMAN OTC DRUG LABEL
Date: 201001004

ACTIVE INGREDIENTS: TRICLOSAN 0.46 mL/100 mL
INACTIVE INGREDIENTS: WATER; SODIUM POLYSTYRENE SULFONATE; DIPROPYLENE GLYCOL; GLYCERIN; SODIUM PYRROLIDONE CARBOXYLATE; AMMONIUM LAURYL SULFATE; COCAMIDOPROPYL BETAINE; HYPROMELLOSE ACETATE SUCCINATE 06081224 (3 MM2/S); SODIUM PHOSPHATE, DIBASIC, DIHYDRATE; CETYL ALCOHOL; ALOE VERA LEAF; CITRIC ACID MONOHYDRATE; METHYLPARABEN; PROPYLPARABEN; FD&C YELLOW NO. 5; FD&C YELLOW NO. 6

Active Ingredient

Triclosan 0.46%

Purpose

Antibacterial

Warnings

For external use only.

When using this product

Avoid contact with eyes. If contact occurs, rinse with water.

Stop using this product and ask doctor if

Irritation or redness develops and lasts

Keep out of reach of children

In case of accidental ingestion, get medical help or contact a Poison Control Center immediately.

Questions or comments?

1 - 800 - 746 - 7287

Uses

For washing to decrease bacteria on the skin

Directions

Pump onto dry hands. Work into lather vigorously. Rinse thoroughly

Inactive Ingredients

Water (Aqua), Sodium Xylenesulfonate, Dipropylene Glycol, Glycerin, Sodium PCA, Ammonium Lauryl Sulfate, Cocamidopropyl Betaine, Polyquaternium-10, Fragrance(Parfum), Disodium Phosphate, Cetyl Alcohol, Aloe barbadensis leaf juice, Citric Acid, Methylparaben, Propylparaben, Yellow 5 (CI 19140), Yellow 6 (CI 15985).

Package Front and Back Labels

cvs8.jpg